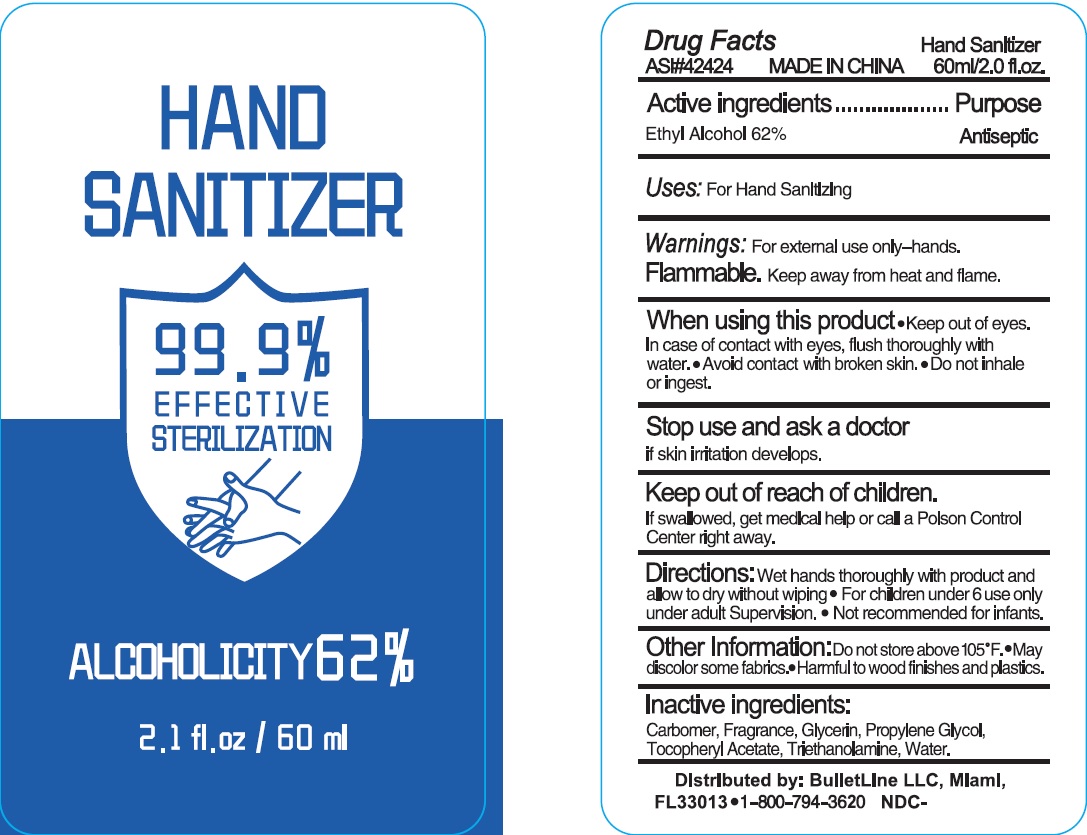 DRUG LABEL: Hand Sanitizer
NDC: 74274-116 | Form: SOLUTION
Manufacturer: Huizhou Bliss Commodity Co., Ltd
Category: otc | Type: HUMAN OTC DRUG LABEL
Date: 20200513

ACTIVE INGREDIENTS: ALCOHOL 62 mL/100 mL
INACTIVE INGREDIENTS: WATER; TROLAMINE; GLYCERIN; PROPYLENE GLYCOL; .ALPHA.-TOCOPHEROL ACETATE, D-; CARBOMER 940

Active ingredient

Ethyl Alcohol 62%

Purpose

Antiseptic

Use

For hand sanitizing

KEEP OUT OF REACH OF CHILDREN

if swallowed, get medical help or contact a Poison Control Center right away.

warnings:

Flamable, keep away from heat and flame

For external use only-hands

When using this product

- keep out of eyes. In case of contact with eyes, flush thoroughly with water
- Avoid contact with broken skin
- Do not inhale or ingest

Stop use and ask a doctor if

skin irritation develops.

Other Information:

- Do not store above 105℃
- May discolor some fabrics
- Harmful to wood finished and plastics.

Directions

- Wet hands thoroughly with product and allow to dry without wiping.
- For children under 6 use only under adult supervision.
- Not recommended for infants.

Inactive ingredients

Carbomer, Fragrance, Glycerin, Propylene Glycol, Tocopheryl Acetate, Triethanolamine, Water